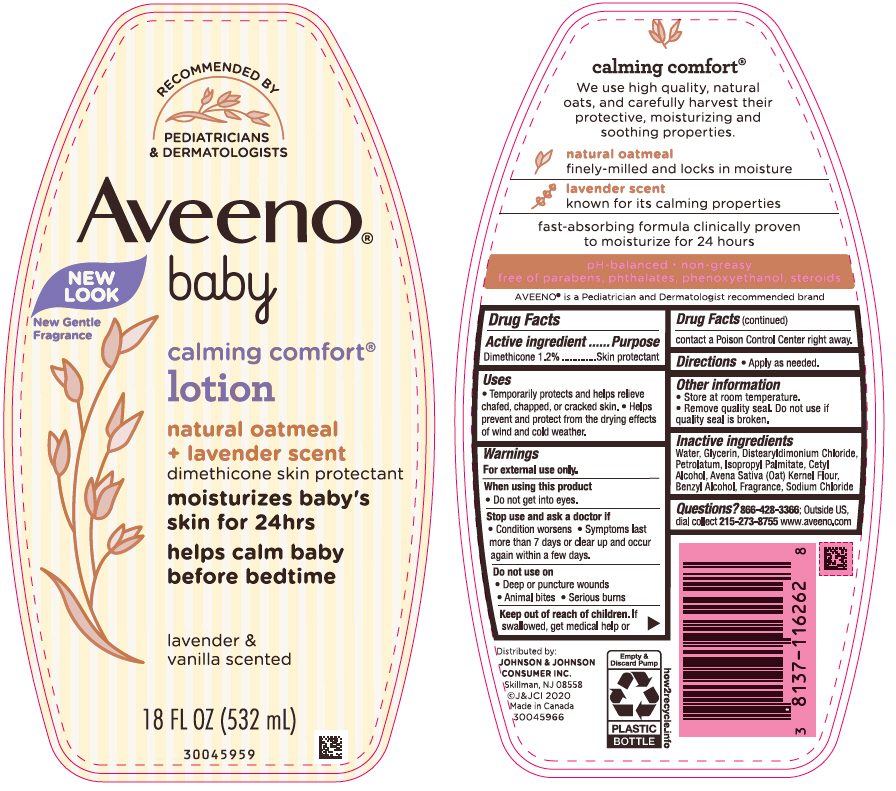 DRUG LABEL: Aveeno Baby Calming Comfort
NDC: 69968-0629 | Form: LOTION
Manufacturer: Kenvue Brands LLC
Category: otc | Type: HUMAN OTC DRUG LABEL
Date: 20241101

ACTIVE INGREDIENTS: DIMETHICONE 12 mg/1 mL
INACTIVE INGREDIENTS: WATER; GLYCERIN; DISTEARYLDIMONIUM CHLORIDE; PETROLATUM; ISOPROPYL PALMITATE; CETYL ALCOHOL; OATMEAL; BENZYL ALCOHOL; SODIUM CHLORIDE

Aveeno Baby Calming Comfort Lotion

Drug Facts

Active ingredient

Dimethicone 1.2%

Purpose

Skin protectant

Uses

- Temporarily protects and helps relieve chafed, chapped, or cracked skin
- Helps prevent and protect from the drying effects of wind and cold weather.

Warnings

For external use only.

When using this product

- Do not get into eyes.

Stop use and ask a doctor if

- Condition worsens
- Symptoms last more than 7 days or clear up and occur again within a few days.

Do not use on

- Deep or puncture wounds
- Animal bites
- Serious burns .

Keep out of reach of children. If swallowed, get medical help or contact a Poison Control Center right away.

Directions

- Apply as needed.

Other information

- Store at room temperature.
- Remove quality seal. Do not use if quality seal is broken.

Inactive ingredients

Water , Glycerin, Distearyldimonium Chloride ,Petrolatum, Isopropyl Palmitate, Cetyl Alcohol, Avena Sativa (Oat) Kernel Flour, Benzyl Alcohol, Fragrance, Sodium Chloride

Questions?

866-428-3366; Outside US, dial collect 215-273-8755 visit www.aveeno.com

Distributed by:
JOHNSON & JOHNSON
CONSUMER INC.
Skillman, NJ 08558

PRINCIPAL DISPLAY PANEL - 532 mL Bottle Label

RECOMMENDED BY
PEDIATRICIANS
& DERMATOLOGIST
Aveeno®
New
Look

baby
New Gentle
Fragrance
calming comfort®
lotion
natural oatmeal
+ lavender scent
dimethicone skin protectant
moisturizes baby's
skin for 24hrs
helps calm baby
before bedtime
lavender &
vanilla scented
18 FL OZ (532 mL)